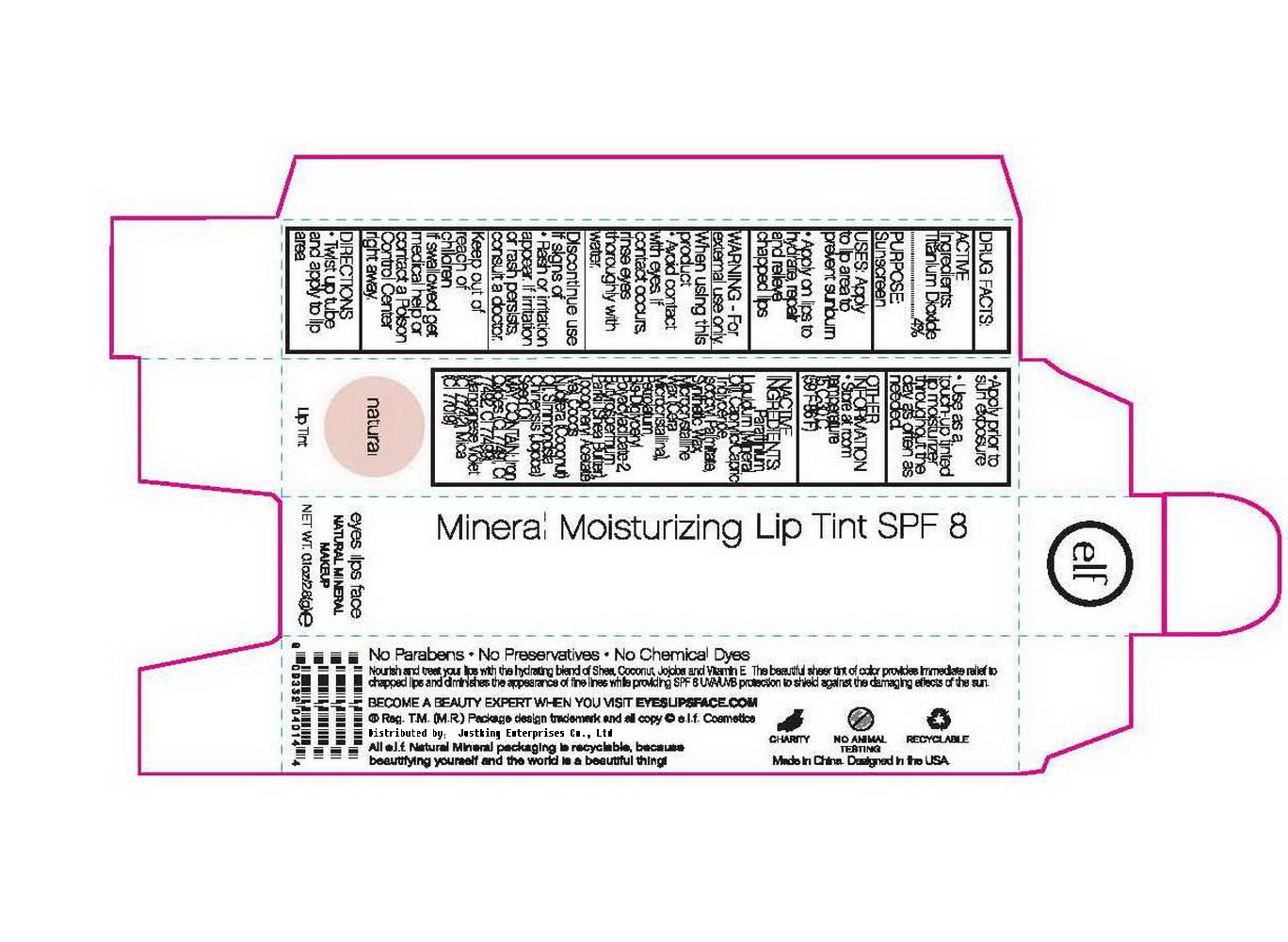 DRUG LABEL: ELF Mineral Moisturizing Lip Tint SPF 8
NDC: 76166-002 | Form: POWDER
Manufacturer: Shanghai Justking Enterprise Co. Ltd.
Category: otc | Type: HUMAN OTC DRUG LABEL
Date: 20110502

ACTIVE INGREDIENTS: TITANIUM DIOXIDE 4 g/100 g
INACTIVE INGREDIENTS: MINERAL OIL; .ALPHA.-TOCOPHEROL ACETATE, DL-; MICA; ETHYLHEXYL PALMITATE; FERRIC OXIDE YELLOW; MICROCRYSTALLINE WAX; MEDIUM-CHAIN TRIGLYCERIDES; PETROLATUM; SHEA BUTTER; COCONUT OIL; JOJOBA OIL

Drug Fact

Active Ingredient:

Titanium Dioxide: 4%

Purpose:

Sunscreen

Uses:

Apply to lip area to prevent Sunburn

Apply on lips to hydrate, repair and relieve chapped lips.

Warning:

For external use only

When Using This Product:

Avoid contact with eyes. If contact occurs, rinse thoroughly with water

ASK DOCTOR

Discontinue use if signs of rash or irritation appear. If irritation or rash persists, consult a doctor.

Keep Out of Reach of Children:

If swallowed get medical help or contact a Poison Control Center immediately

Directions:

Twist up tube and apply to lip area.

Apply prior to sun exposure

Use as a touch-up tinted lip moisturizer throughout the day as often as needed.

STORAGE AND HANDLING

Other Imformation:

Store at room temperature 15-30C (59-86F)

Inactive Ingredient:

Paraffinium Liquidum (Mineral Oil), Caprylic/Capric Triglyceride, Iso-Octyl Palmitate, Synthetic Wax, Microcrystalline Wax, Petrolatum, Bis-Diglyceryl Polyacyladipate-2, Butyrospermum Parkli (Shea Butter), Tocopheryl Acetate, Cocos Nucifere (Coconut) Oil, Simmondsia Chinensis (Jojoba) Seed Oil.

May contain:

Iron Oxides (CI 77491, CI 77492, CI 77499), Manganese Violet (CI 77742), Mica (CI 77019)

label